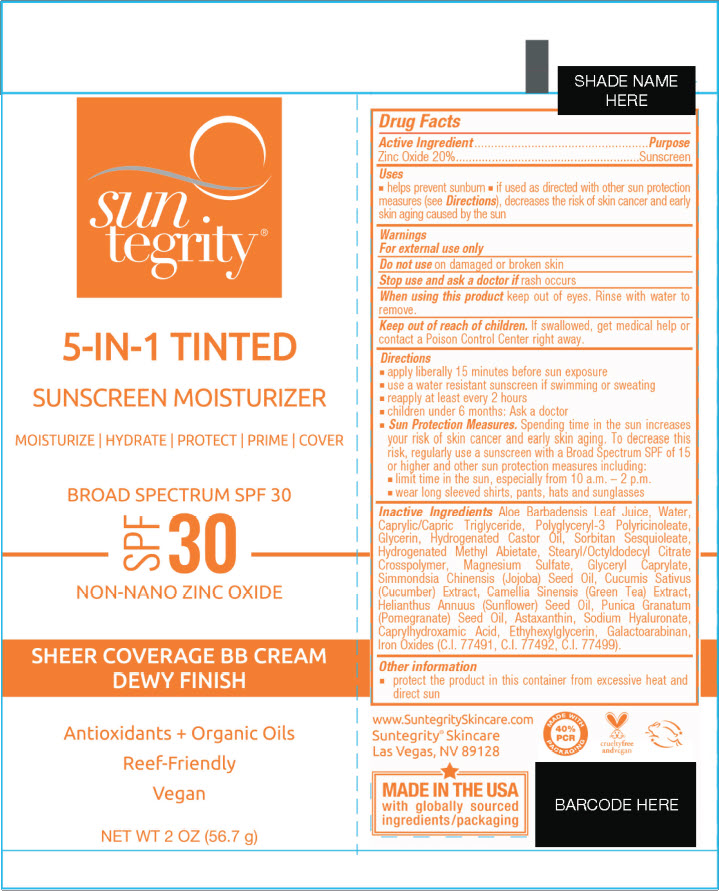 DRUG LABEL: 5-IN-1 TINTED FACE SUNSCREEN - FAIR
NDC: 69949-051 | Form: CREAM
Manufacturer: Synchronicity Spa, Inc. DBA Suntegrity
Category: otc | Type: HUMAN OTC DRUG LABEL
Date: 20250604

ACTIVE INGREDIENTS: ZINC OXIDE 200 mg/1 g
INACTIVE INGREDIENTS: ALOE VERA LEAF; WATER; MEDIUM-CHAIN TRIGLYCERIDES; POLYGLYCERYL-3 RICINOLEATE; GLYCERIN; HYDROGENATED CASTOR OIL; SORBITAN SESQUIOLEATE; HYDROGENATED METHYL ABIETATE; STEARYL/OCTYLDODECYL CITRATE CROSSPOLYMER; MAGNESIUM SULFATE, UNSPECIFIED FORM; GLYCERYL MONOCAPRYLATE; JOJOBA OIL; CUCUMBER; GREEN TEA LEAF; SUNFLOWER OIL; POMEGRANATE SEED OIL; ASTAXANTHIN; HYALURONATE SODIUM; CAPRYLHYDROXAMIC ACID; ETHYLHEXYLGLYCERIN; GALACTOARABINAN; FERROSOFERRIC OXIDE; FERRIC OXIDE RED; FERRIC OXIDE YELLOW

5-IN-1 TINTED FACE SUNSCREEN

Drug Facts

Active Ingredient

Zinc Oxide 20%

Purpose

Sunscreen

Uses

- helps prevent sunburn
- if used as directed with other sun protection measures (see Directions), decreases the risk of skin cancer and early skin aging caused by the sun

Warnings

For external use only

Do not use on damaged or broken skin

Stop use and ask a doctor if rash occurs

When using this product keep out of eyes. Rinse with water to remove.

Keep out of reach of children. If swallowed, get medical help or contact a Poison Control Center right away.

Directions

- apply liberally 15 minutes before sun exposure
- use a water resistant sunscreen if swimming or sweating
- reapply at least every 2 hours
- children under 6 months: Ask a doctor
- Sun Protection Measures. Spending time in the sun increases your risk of skin cancer and early skin aging. To decrease this risk, regularly use a sunscreen with a Broad Spectrum SPF of 15 or higher and other sun protection measures including:
  - limit time in the sun, especially from 10 a.m. – 2 p.m.
  - wear long sleeved shirts, pants, hats and sunglasses

Inactive Ingredients

Aloe Barbadensis Leaf Juice, Water, Caprylic/Capric Triglyceride, Polyglyceryl-3 Polyricinoleate, Glycerin, Hydrogenated Castor Oil, Sorbitan Sesquioleate, Hydrogenated Methyl Abietate, Stearyl/Octyldodecyl Citrate Crosspolymer, Magnesium Sulfate, Glyceryl Caprylate, Simmondsia Chinensis (Jojoba) Seed Oil, Cucumis Sativus (Cucumber) Extract, Camellia Sinensis (Green Tea) Extract, Helianthus Annuus (Sunflower) Seed Oil, Punica Granatum (Pomegranate) Seed Oil, Astaxanthin, Sodium Hyaluronate, Caprylhydroxamic Acid, Ethyhexylglycerin, Galactoarabinan, Iron Oxides (C.I. 77491, C.I. 77492, C.I. 77499).

Other information

- protect the product in this container from excessive heat and direct sun

PRINCIPAL DISPLAY PANEL - 56.7 g Tube Label - Fair

sun
tegrity®

5-IN-1 TINTED
SUNSCREEN MOISTURIZER

MOISTURIZE | HYDRATE | PROTECT | PRIME | COVER

BROAD SPECTRUM SPF 30

SPF
30

NON-NANO ZINC OXIDE

SHEER COVERAGE BB CREAM
DEWY FINISH

Antioxidants + Organic Oils
Reef-Friendly
Vegan

NET WT 2 OZ (56.7 g)

PRINCIPAL DISPLAY PANEL - 56.7 g Tube Label - Light

sun
tegrity®

5-IN-1 TINTED
SUNSCREEN MOISTURIZER

MOISTURIZE | HYDRATE | PROTECT | PRIME | COVER

BROAD SPECTRUM SPF 30

SPF
30

NON-NANO ZINC OXIDE

SHEER COVERAGE BB CREAM
DEWY FINISH

Antioxidants + Organic Oils
Reef-Friendly
Vegan

NET WT 2 OZ (56.7 g)

PRINCIPAL DISPLAY PANEL - 56.7 g Tube Label - Golden Light

sun
tegrity®

5-IN-1 TINTED
SUNSCREEN MOISTURIZER

MOISTURIZE | HYDRATE | PROTECT | PRIME | COVER

BROAD SPECTRUM SPF 30

SPF
30

NON-NANO ZINC OXIDE

SHEER COVERAGE BB CREAM
DEWY FINISH

Antioxidants + Organic Oils
Reef-Friendly
Vegan

NET WT 2 OZ (56.7 g)

PRINCIPAL DISPLAY PANEL - 56.7 g Tube Label - Medium

sun
tegrity®

5-IN-1 TINTED
SUNSCREEN MOISTURIZER

MOISTURIZE | HYDRATE | PROTECT | PRIME | COVER

BROAD SPECTRUM SPF 30

SPF
30

NON-NANO ZINC OXIDE

SHEER COVERAGE BB CREAM
DEWY FINISH

Antioxidants + Organic Oils
Reef-Friendly
Vegan

NET WT 2 OZ (56.7 g)